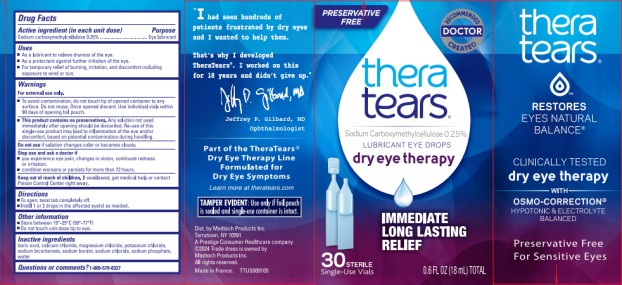 DRUG LABEL: TheraTears Lubricant
NDC: 58790-000 | Form: SOLUTION/ DROPS
Manufacturer: MEDTECH PRODUCTS INC
Category: otc | Type: HUMAN OTC DRUG LABEL
Date: 20251023

ACTIVE INGREDIENTS: CARBOXYMETHYLCELLULOSE SODIUM, UNSPECIFIED FORM 2.5 mg/1 mL
INACTIVE INGREDIENTS: BORIC ACID; CALCIUM CHLORIDE; MAGNESIUM CHLORIDE; POTASSIUM CHLORIDE; SODIUM BICARBONATE; SODIUM CHLORIDE; SODIUM BORATE; WATER; SODIUM PHOSPHATE

TheraTears PF 58790-000

THERATEARS LUBRICANT- carboxymethylcellulose sodium solution/ drops
Medtech Products Inc., a Prestige Consumer Healthcare company

Disclaimer: Most OTC drugs are not reviewed and approved by FDA, however they may be marketed if they comply with applicable regulations and policies. FDA has not evaluated whether this product complies.

----------

Drug Facts

Active ingredient (In each unit dose)

Sodium Carboxymethylcellulose 0.25%

Purpose

Eye lubricant

Uses

- As a lubricant to relieve dryness of the eye.
- As a protectant against further irritation of the eye.
- For temporary relief of burning, irritation, and discomfort including exposure to wind or sun.

Warnings

For external use only

- To avoid contamination do not touch tip of opened container to any surface. Do not reuse. Once opened discard. Use individual vials within 90 days of opening foil pouch.
- This product contains no preservatives. Any solution not used immediately after opening should be discarded. Re-use of this single-use product may lead to inflammation of the eye and/or discomfort, based on potential contamination during handling.

Do not use

- If solution changes color or becomes cloudy.

Stop use and ask a doctor if

- You experience eye pain, changes in vision, continued redness or irritation.
- Condition worsens or persists for more than 72 hours.

Keep out of reach of children.

If swallowed, get medical help or contact a Poison Control Center immediately.

Directions

- To open, twist tab completely off.
- Instill 1 or 2 drops in the affected eye(s) as needed.

Other information

- Store between 15-25 C (59-77F)
- Do not touch unit-dose tip to eye.

Inactive ingredients

boric acid , calcium chloride, magnesium chloride, potassium chloride, sodium bicarbonate, sodium borate, sodium chloride, sodium phosphate, water

Questions and comments?

1-800-579-8327

Principal Display Panel

PRESERVATIVE FREE

thera

tears®

THERAPY FOR YOUR EYES TM

dry eye therapy

LUBRICANT

EYE DROPS

IMMEDIATE

LONG LASTING

RELIEF

30 STERILE Single-Use Vials

0.60 FL OZ (18.0mL) TOTAL